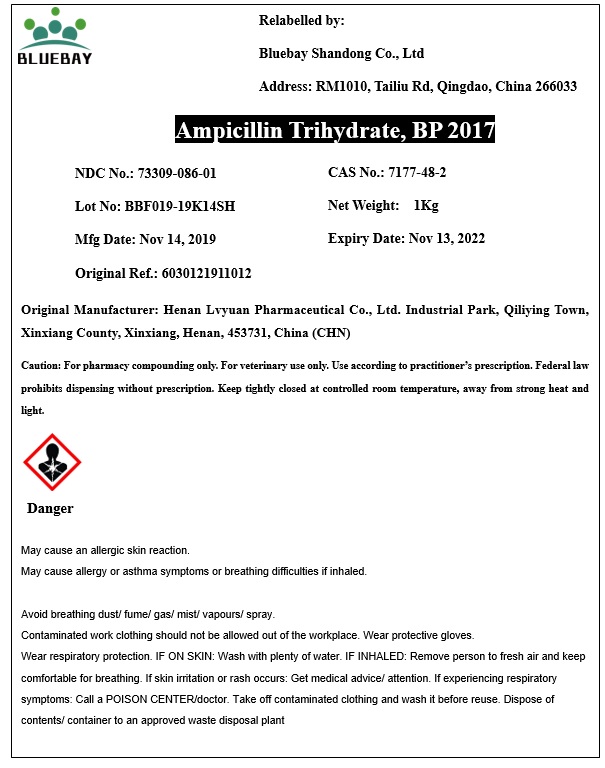 DRUG LABEL: Ampicillin Trihydrate
NDC: 73309-086 | Form: POWDER
Manufacturer: BLUEBAY SHANDONG CO.,LTD
Category: other | Type: BULK INGREDIENT
Date: 20200120

ACTIVE INGREDIENTS: Ampicillin Trihydrate 1 kg/1 kg

Ampicillin Trihydrate